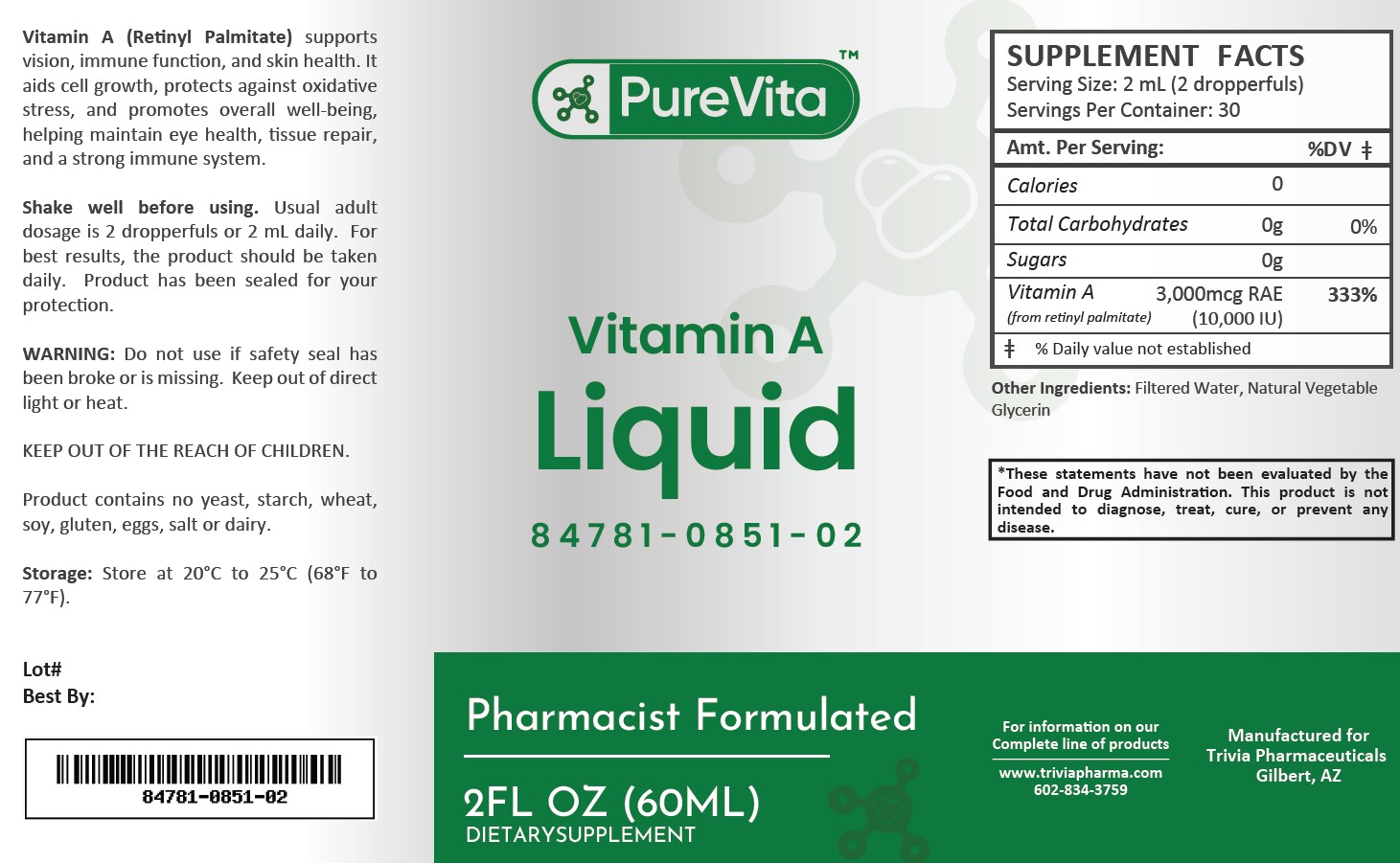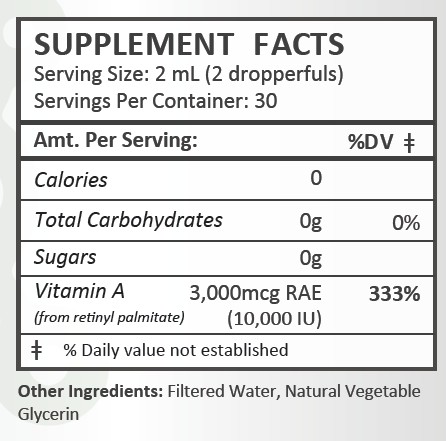 DRUG LABEL: PureVita Vitamin A
NDC: 84781-851 | Form: LIQUID
Manufacturer: Trivia Pharmaceuticals, LLC
Category: other | Type: Dietary Supplement
Date: 20250306

ACTIVE INGREDIENTS: RETINYL ACETATE 3000 ug/2 mL

PureVita Vitamin A

Health Claim:

PureVita Vitamin A Liquid:

Description:

PureVita Vitamin A (Retinyl Palmitate) supports vision, immune funtion and skin health. It aids cell growth, protects against oxidative stress, and promotes overall well-being, helping maintain eye health, tissue repair, and a strong immune system.

This listed product is not a National Drug Code, but instead has merely been formatted to comply with standard industry practice for pharmacy and insurance computer systems.

Warnings Section:

Do not use if safety seal has been broken or is missing. Keep out of direct light or heat.

KEEP OUT OF THE REACH OF CHILDREN.

Product contains no yeast, starch, wheat, soy, gluten, eggs, salt or dairy.

Dosage and Administration:

Usual adult dose is 2 dropperfuls or 2 mL daily. For the best results, the product should be taken daily. Product has been sealed for your protection.

How Supplied:

PureVita Vitamin A Liquid is supplied as white, clear liquid.

84781-0851-02

Reserved for Professional Recommendation: All prescriptions using this product shall be pursuant to state statutes as applicable. This is not an Orange Book product. There are no implied or explicit claims on therapeutic equivalence.

Manufactured for:

Trivia Pharmaceuticals

Gilbert, AZ

Storage:

Storage: Store at 20oC to 25oC (68oF to 77oF). Keep refrigerated after opening.